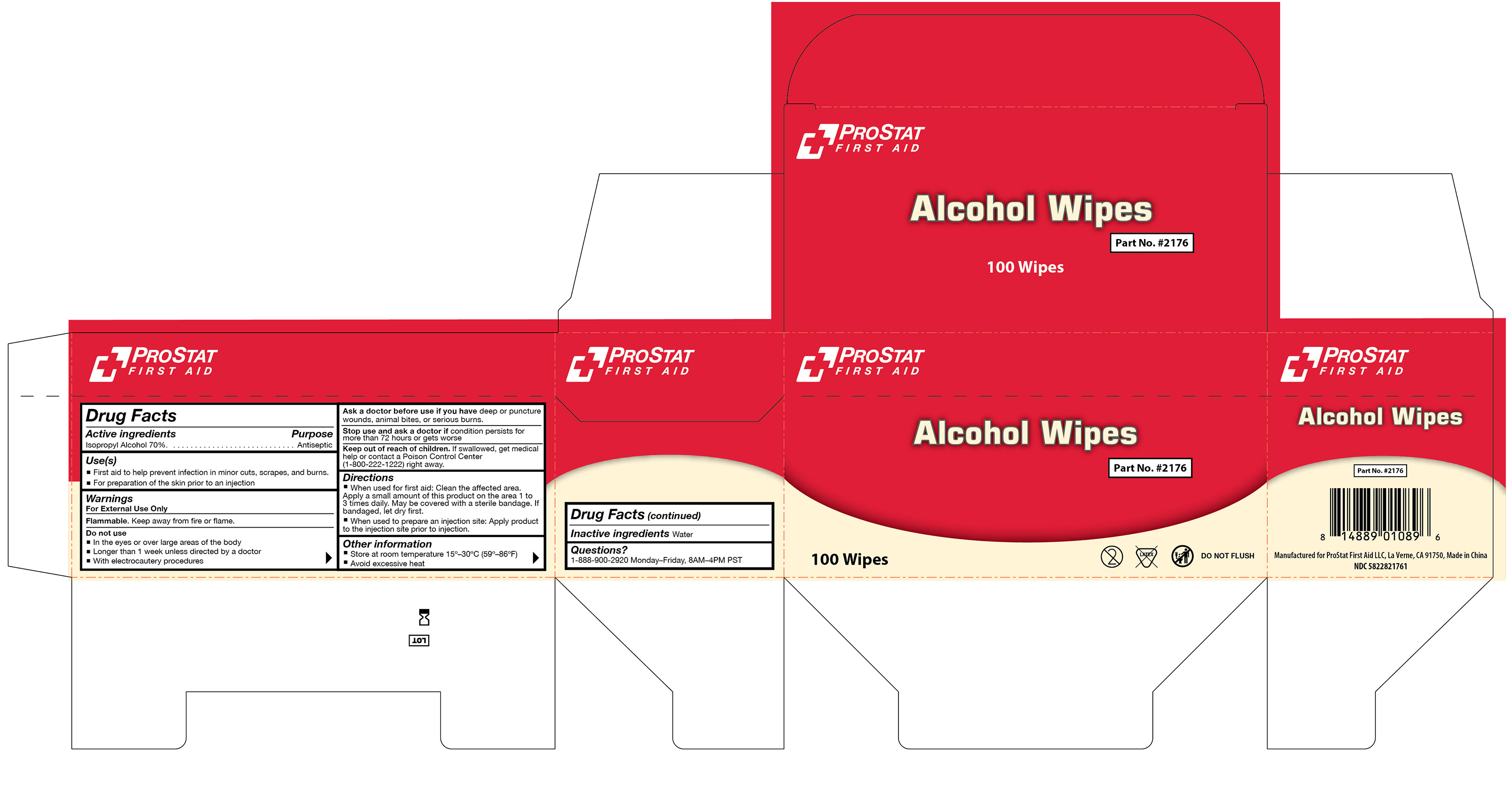 DRUG LABEL: Alcohol Wipes
NDC: 58228-2176 | Form: SWAB
Manufacturer: ProStat First Aid LLC
Category: otc | Type: HUMAN OTC DRUG LABEL
Date: 20251215

ACTIVE INGREDIENTS: ISOPROPYL ALCOHOL 0.7 mL/1 mL
INACTIVE INGREDIENTS: WATER

PS-2176

Active Ingredient

Isopropyl Alcohol 70%

Purpose

Antiseptic

Use(s)

• First aid to help prevent infection in minor cuts, scrapes, and burns

• For preparation of the skin prior to an injection

Warnings

For External Use only

Flammable. Keep away from fire or flame.

Do not use

• In the eyes or over large areas of the body

• Longer than 1 week unless directed by a doctor

• With electrocautery procedures

Ask a doctor before use if you have

deep or puncture wounds, animal bites, or serious burns.

Stop use and ask a doctor if

condition persists for more than 72 hours or gets worse.

Keep out of reach of children

If swallowed, get medical help or contact a Poison Control Center (1-800-222-1222) right away.

Directions

• When used for first aid: Clean the affected area. Apply a small amount of this product on the area 1 to 3 times a day. May be covered with a sterile bandage. If bandaged, let dry first.

• When used to prepare an injection site: Apply product to the injection site prior to injection.

Inactive ingredients

Water

Other information

• Store at room temperature 15º-30ºC (59º-86ºF)

• Avoid excessive heat

Questions?

1-888-900-2920 Monday-Friday, 8AM-4PM PST

Label

PS-2176